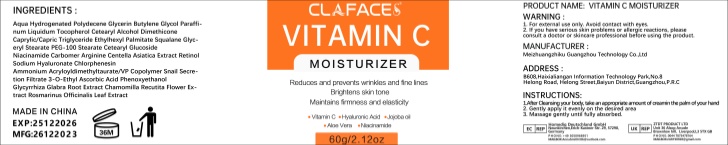 DRUG LABEL: CLAFACES VITAMIN C MOISTURIZER
NDC: 84350-066 | Form: CREAM
Manufacturer: Shenzhen Sihai Juntong Technology Co., LTD
Category: otc | Type: HUMAN OTC DRUG LABEL
Date: 20240814

ACTIVE INGREDIENTS: SQUALANE 1 g/100 mg
INACTIVE INGREDIENTS: WATER

ACTIVE INGREDIENT

Glycerin 5%

INACTIVE INGREDIENT

AQUA 5%

PURPOSE

Moisturizing

Warning

WARNING:1.For external use only,Avoid contact with eyes.2.lf you have serious skin problems or allergic reactions,please consult a doctor or skin care professional before using the product.

Do not use

If you have allergic reactions, stop to use

When using this product

1.After cleansing the body, take an appropriate amount of foot cream on the palm of your hand

2.Gently apply it evenly on the desired area

3.Massage gently until fully absorbed

Keep out of reach of children

use

INSTRUCTIONS:
1.After cleansing the body, take an appropriate amount of foot cream on the palm of your hand

2.Gently apply it evenly on the desired area
3.Massage gently until fully absorbed

Dosage and administration

appropnate amount

PRINCIPAL DISPLAY PANEL

60g NDC:84350-066-01